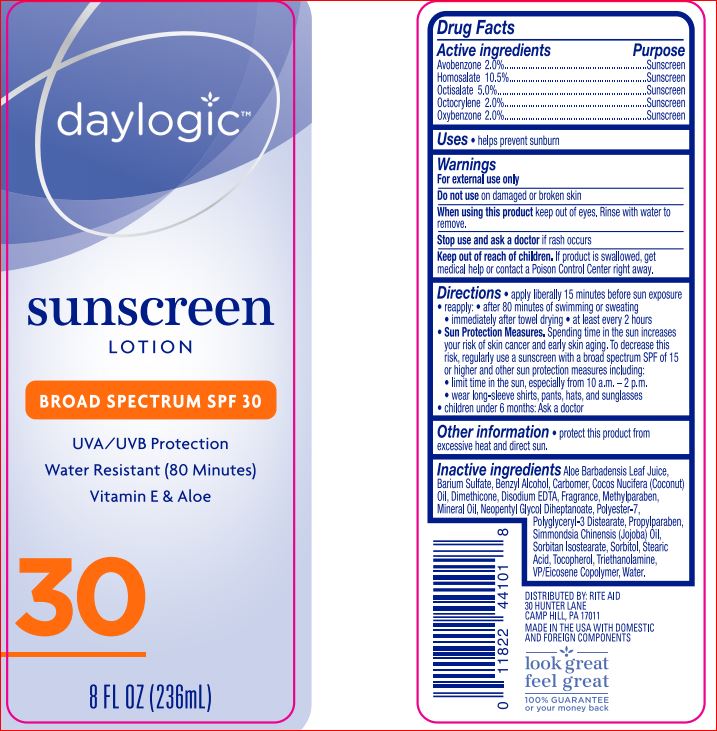 DRUG LABEL: Sunscreen SPF 30
NDC: 11822-1113 | Form: LOTION
Manufacturer: Rite Aid
Category: otc | Type: HUMAN OTC DRUG LABEL
Date: 20180514

ACTIVE INGREDIENTS: Avobenzone 2 mg/100 mL; Homosalate 10.5 mg/100 mL; Octisalate 5 mg/100 mL; Octocrylene 2 mg/100 mL; Oxybenzone 2 mg/100 mL
INACTIVE INGREDIENTS: ALOE VERA LEAF; Barium Sulfate; Benzyl Alcohol; CARBOMER 940; COCONUT OIL; Dimethicone; EDETATE DISODIUM; Methylparaben; Mineral Oil; Neopentyl Glycol Diheptanoate; Polyester-7; Polyglyceryl-3 Distearate; Propylparaben; JOJOBA OIL; Sorbitan Isostearate; Sorbitol; Stearic Acid; Tocopherol; TROLAMINE; VINYLPYRROLIDONE/EICOSENE COPOLYMER; Water

Drug Facts

Active ingredients Purpose
Avobenzone 2.00%...............................................................Sunscreen
Homosalate 10.50%..............................................................Sunscreen
Octisalate 5.00%...................................................................Sunscreen
Octocrylene 2.00%................................................................Sunscreen
Oxybenzone 2.00%...............................................................Sunscreen

INDICATIONS AND USAGE

Uses • helps prevent sunburn

Warnings
For external use only
Do not use on damaged or broken skin
When using this product keep out of eyes. Rinse with water to remove.
Stop use and ask a doctor if rash occurs

DOSAGE AND ADMINISTRATION

Directions • apply liberally 15 minutes before sun exposure
• reapply: • after 80 minutes of swimming or sweating
• immediately after towel drying • at least every 2 hours
• Sun Protection Measures. Spending time in the sun increases your
risk of skin cancer and early skin aging. To decrease this risk,
regularly use a sunscreen with a broad spectrum SPF of 15 or higher
and other sun protection measures including:
• limit time in the sun, especially from 10 a.m. – 2 p.m.
• wear long-sleeve shirts, pants, hats, and sunglasses
• children under 6 months: Ask a doctor

Inactive ingredients

Aloe Barbadensis Leaf Juice
Barium Sulfate
Benzyl Alcohol
Carbomer
Cocos Nucifera (Coconut) Oil
Dimethicone
Disodium EDTA
Fragrance
Methylparaben
Mineral Oil
Neopentyl Glycol Diheptanoate
Polyester-7
Polyglyceryl-3 Distearate
Propylparaben
Simmondsia Chinensis (Jojoba) Oil
Sorbitan Isostearate
Sorbitol
Stearic Acid
Tocopherol
Triethanolamine
VP/Eicosene Copolymer
Water